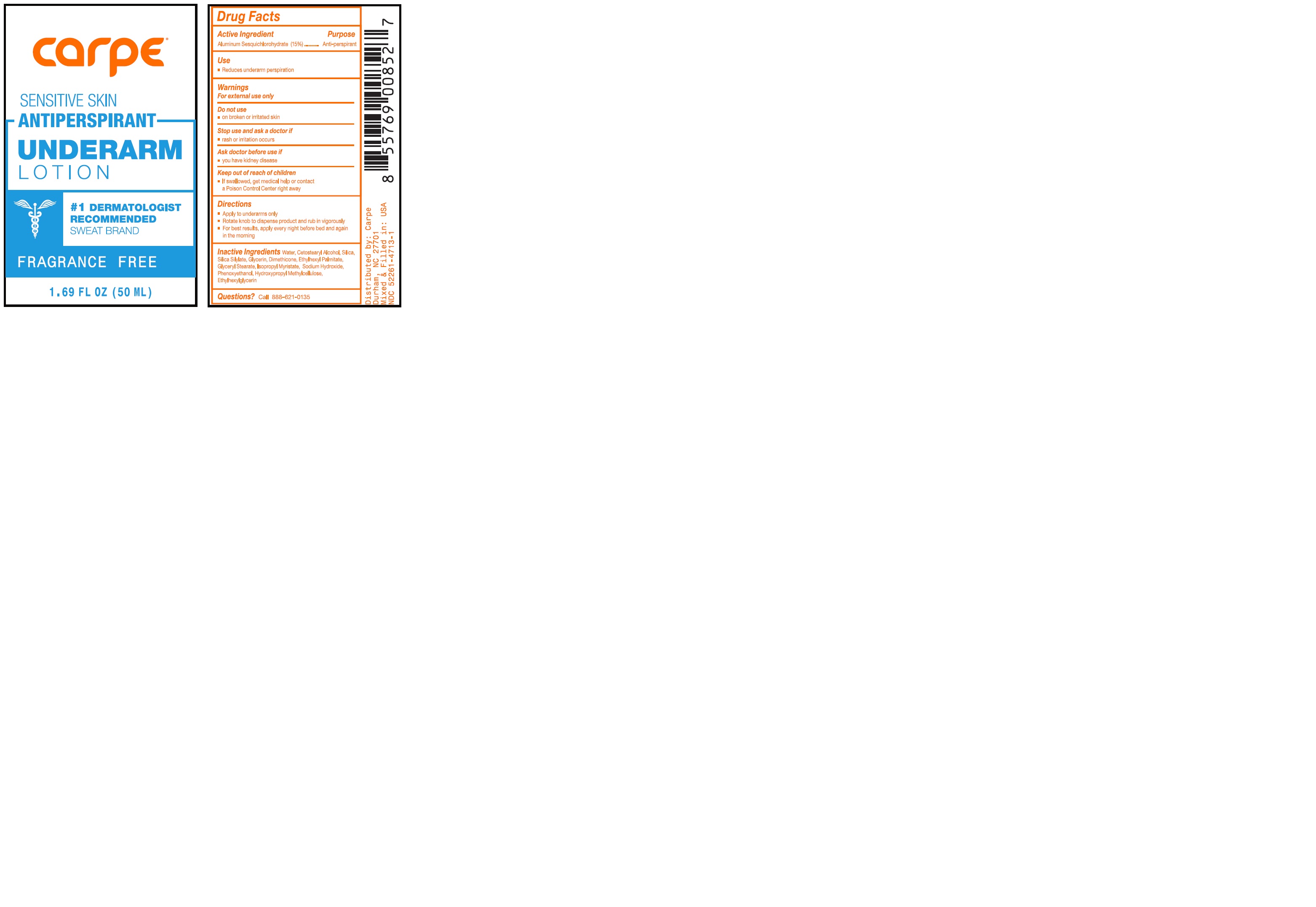 DRUG LABEL: Carpe Antiperspirant Underarm Fragrance Free
NDC: 52261-4713 | Form: Lotion
Manufacturer: Cosco International, Inc.
Category: otc | Type: HUMAN OTC DRUG LABEL
Date: 20250206

ACTIVE INGREDIENTS: Aluminum Sesquichlorohydrate 0.15 kg/1 kg
INACTIVE INGREDIENTS: WATER; CETOSTEARYL ALCOHOL; SILICON DIOXIDE; HEXAMETHYLDISILAZANE; GLYCERIN; ETHYLHEXYL PALMITATE; DIMETHICONE 350; GLYCERYL STEARATE SE; PHENOXYETHANOL; ISOPROPYL MYRISTATE; SODIUM HYDROXIDE; HYPROMELLOSE 2208 (100000 MPA.S); ETHYLHEXYLGLYCERIN

Drug Facts

Active Ingredient Purpose
Aluminum Sesquicholorhydrate 15% .......................Anti-perspirant

PURPOSE

Anti-perspirant

Use

- Reduces underarm perspiration

Warnings

For external use only

Do not use

- on broken or irritated skin

Stop use and ask a doctor if

- rash or irritation occurs

Ask doctor before use if

- you have kidney disease

Keep out of reach of children

- If swallowed, get medical help or contact a Poison Control Center right away

Directions

- Apply to underarms only
- Rotate knob to dispense product and rub in vigorously
- For best results, apply every night before bed and again in the morning

Inactive ingredients

Water, Cetostearyl Alcohol, Silica, Silica Silylate, Glycerin, Dimethicone, Ethylhexyl Palmitate, Glyceryl Stearate, Isopropyl Myristate, Sodium Hydroxide, Phenoxyethanol, Hydroxypropyl Methylcellulose, Ethylhexylglycerin

Questions?

Call 888-621-0135